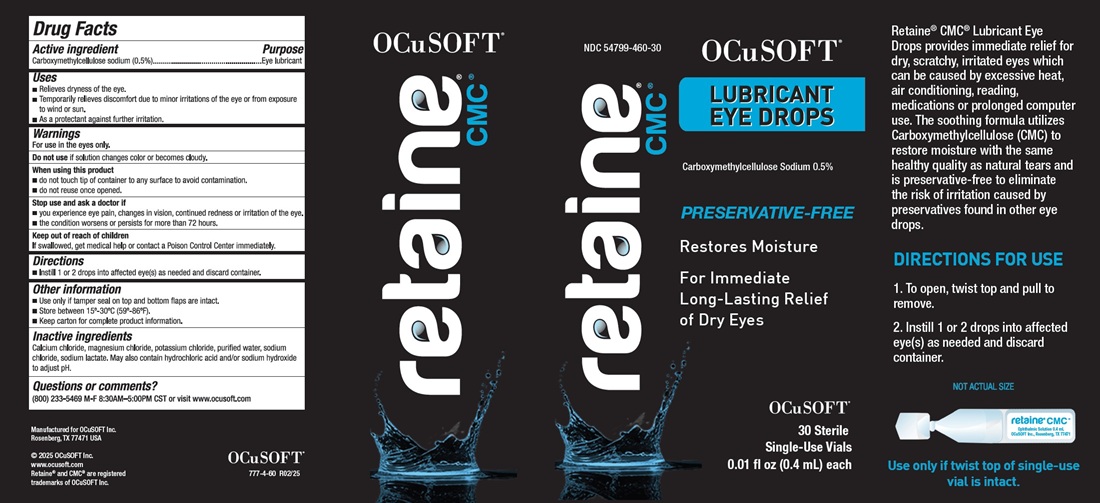 DRUG LABEL: Retaine CMC
NDC: 54799-460 | Form: SOLUTION/ DROPS
Manufacturer: OCuSOFT INC.
Category: otc | Type: HUMAN OTC DRUG LABEL
Date: 20250221

ACTIVE INGREDIENTS: CARBOXYMETHYLCELLULOSE SODIUM, UNSPECIFIED 5 mg/1 mL
INACTIVE INGREDIENTS: Calcium Chloride; Magnesium Chloride; Potassium Chloride; Water; Sodium Chloride; Sodium Lactate; Hydrochloric Acid; Sodium Hydroxide

Retaine® CMC® Lubricant Eye Drops
Drug Facts

Active ingredient

Carboxymethylcellulose sodium (0.5%)

Purpose

Eye lubricant

Uses

- Relieves dryness of the eye.
- Temporarily relieves discomfort due to minor irritations of the eye or from exposure to wind or sun.
- As a protectant against further irritation.

Warnings

For use in the eyes only.

Do not use

if solution changes color or becomes cloudy.

When using this product

- do not touch tip of container to any surface to avoid contamination.
- do not reuse once opened.

Stop use and ask a doctor if

- you experience eye pain, changes in vision, continued redness or irritation of the eye.
- the condition worsens or persists for more than 72 hours.

Keep out of reach of children

If swallowed, get medical help or contact a Poison Control Center immediately.

Directions

- Instill 1 or 2 drops into affected eye(s) as needed and discard container.

Other information

- Use only if tamper seal on top and bottom flaps are intact.
- Store between 15°-30°C (59°-86°F).
- Keep carton for complete product information.

Inactive ingredients

Calcium chloride, magnesium chloride, potassium chloride, purified water, sodium chloride, sodium lactate. May also contain hydrochloric acid and/or sodium hydroxide to adjust pH.

Questions or comments?

(800) 233-5469 M-F 8:30-5:00PM CST or visit www.ocusoft.com

PACKAGE LABEL.PRINCIPAL DISPLAY PANEL

NDC 54799-460-30
OCuSOFT®
LUBRICANT
EYE DROPS
Carboxymethylcellulose Sodium 0.5%
PRESERVATIVE-FREE
Restores Moisture
For Immediate
Long-Lasting Relief
of Dry Eyes
OCuSOFT®
30 Sterile
Single-Use Vials
0.01 fl oz (0.4 mL) each
Retaine® CMC® Lubricant Eye
Drops provides immediate relief for
dry, scratchy, irritated eyes which
can be caused by excessive heat,
air conditioning, reading,
medications or prolonged computer
use. The soothing formula utilizes
Carboxymethylcellulose (CMC) to
restore moisture with the same
healthy quality as natural tears and
is preservative-free to eliminate
the risk of irritation caused by
preservatives found in other eye
drops.
DIRECTIONS FOR USE
1. To open, twist top and pull to
remove.
2. Instill 1 or 2 drops into affected
eye(s) as needed and discard
container.
NOT ACTUAL SIZE
Use only if twist top of single-use
vial is intact.
Manufactured for OCuSOFT Inc.
Rosenberg, TX 77471 USA
© 2024 OCuSOFT Inc.
www.ocusoft.com
Retaine® and CMC® are registered
trademarks of OCuSOFT Inc.
777-4-60 R02/25